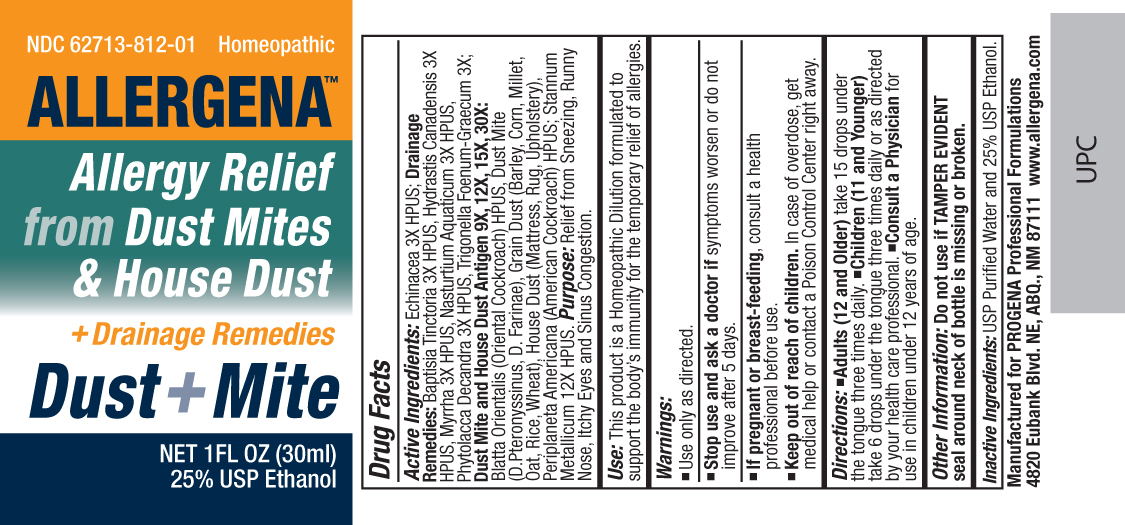 DRUG LABEL: Allergena
NDC: 62713-812 | Form: LIQUID
Manufacturer: Meditrend, Inc. DBA Progena Professional Formulations
Category: homeopathic | Type: HUMAN OTC DRUG LABEL
Date: 20151125

ACTIVE INGREDIENTS: ECHINACEA, UNSPECIFIED 3 [hp_X]/1 mL; BAPTISIA TINCTORIA ROOT 3 [hp_X]/1 mL; GOLDENSEAL 3 [hp_X]/1 mL; MYRRH 3 [hp_X]/1 mL; NASTURTIUM OFFICINALE 3 [hp_X]/1 mL; PHYTOLACCA AMERICANA ROOT 3 [hp_X]/1 mL; FENUGREEK LEAF 3 [hp_X]/1 mL; BLATTA ORIENTALIS 30 [hp_X]/1 mL; DERMATOPHAGOIDES PTERONYSSINUS 30 [hp_X]/1 mL; DERMATOPHAGOIDES FARINAE 30 [hp_X]/1 mL; BARLEY 30 [hp_X]/1 mL; CORN 30 [hp_X]/1 mL; MILLET 30 [hp_X]/1 mL; OAT 30 [hp_X]/1 mL; BROWN RICE 30 [hp_X]/1 mL; WHEAT BRAN 30 [hp_X]/1 mL; HOUSE DUST 30 [hp_X]/1 mL; PERIPLANETA AMERICANA 30 [hp_X]/1 mL; TIN 12 [hp_X]/1 mL
INACTIVE INGREDIENTS: WATER; ALCOHOL

Dust + Mite

ACTIVE INGREDIENT

Active Ingredients:Echinacea 3X HPUS; Drainage Remedies:Baptisia Tinctoria 3X HPUS, Hydrastis Canadensis 3X HPUS, Myrrha 3X HPUS, Nasturtium Aquaticum 3X HPUS, Phytolacca Decandra 3X HPUS, Trigonella Foenum-Graecum 3X; Dust Mite and House Dust Antigen 9X, 12X, 15X, 30X:Blatta Orientalis (Oriental Cockroach) HPUS, Dust Mite (D.Pteronyssinus, D. Farinae), Grain Dust (Barley, Corn, Millet, Oat, Rice, Wheat), House Dust (Mattress, Rug, Upholstery), Periplaneta Americana (American Cockroach) HPUS; Stannum Metallicum 12X HPUS.

PURPOSE

Purpose:Relief from Sneezing, Runny Nose, Itchy Eyes and Sinus Congestion.

INDICATIONS AND USAGE

Use:This product is a Homeopathic Dilution formulated to support the body's immunity for the temporary relief of allergies.

Keep Out of Reach of Children. In case of overdose, get medical help or contact a
Poison Control Center right away.

Warnings:

- Use Only as directed.
- Stop use and ask a doctor ifsymptoms worsen or do not improve after 5 days.
- If pregnant or breast-feeding, consult a health professional before use.

DOSAGE AND ADMINISTRATION

Directions:• Shake Well Before Use.• Adults (12 and Older)take 15 drops under the tongue three times daily.• Children (11 and Younger)take 6 drops under the tongue three times daily or as directed by your health care professional.• Consult a Physicianfor use in children under 12 years of age.

Other Information: Do not use if TAMPER EVIDENT seal around neck of bottle is missing or broken.

Inactive Ingredients:Demineralized water and 25% USP Ethanol.

PACKAGE LABEL

Manufactured for Progena Professional Formulations
4820 Eubank Blvd. NE, ABQ, NM 87111, www.allergena.com